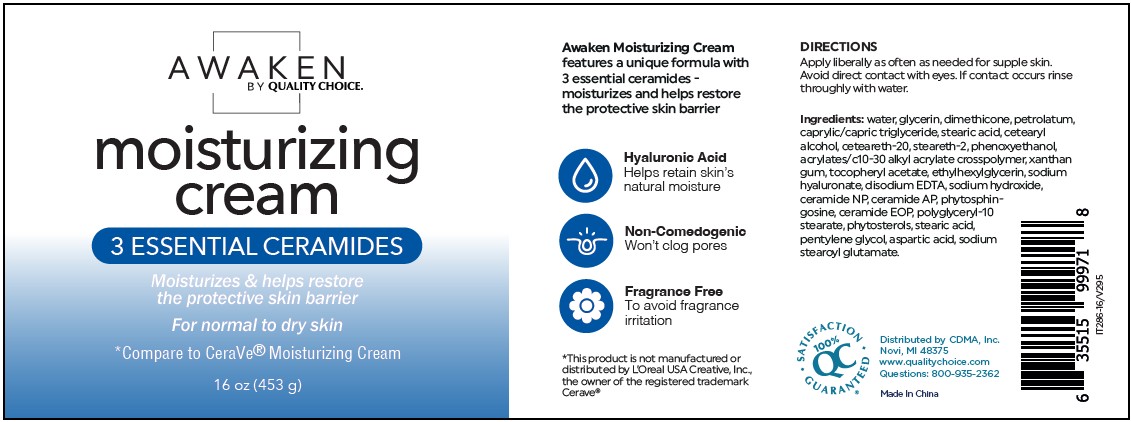 DRUG LABEL: Awaken Moisturizing Cream
NDC: 75376-104 | Form: CREAM
Manufacturer: Guangzhou Danting Bath&Body Care Industry Co. Ltd
Category: otc | Type: HUMAN OTC DRUG LABEL
Date: 20250821

ACTIVE INGREDIENTS: DIMETHICONE 5 g/100 g
INACTIVE INGREDIENTS: WATER; GLYCERIN; PETROLATUM; CAPRYLIC/CAPRIC TRIGLYCERIDE; STEARIC ACID; CETEARYL ALCOHOL; CETEARETH-20; STEARETH-2; PHENOXYETHANOL; ACRYLATES/C10-30 ALKYL ACRYLATE CROSSPOLYMER (60000 MPA.S); XANTHAN GUM; ALPHA-TOCOPHEROL ACETATE; ETHYLHEXYLGLYCERIN; SODIUM HYALURONATE; EDETATE DISODIUM; SODIUM HYDROXIDE; CERAMIDE NP; CERAMIDE AP; PHYTOSPHINGOSINE; CERAMIDE 1; POLYGLYCERYL-10 STEARATE; PENTYLENE GLYCOL; ASPARTIC ACID; SODIUM STEAROYL GLUTAMATE

Awaken Moisturizing Cream Danting-MGC-CDMA

Active Ingredient

Dimethicone 5%

PURPOSE

Skin Protectant

DOSAGE AND ADMINISTRATION

Skin Protectant

WHEN USING

Avoid direct contact with eyes. If contact occurs rinse
throughly with water.

INDICATIONS AND USAGE

Apply liberally as often as needed for supple skin.
Avoid direct contact with eyes. If contact occurs rinse
throughly with water.

STORAGE AND HANDLING

Store in a cool, dark place

INACTIVE INGREDIENT

water, glycerin, dimethicone, petrolatum,
caprylic/capric triglyceride, stearic acid, cetearyl
alcohol, ceteareth-20, steareth-2, phenoxyethanol,
acrylates/c10-30 alkyl acrylate crosspolymer, xanthan
gum, tocopheryl acetate, ethylhexylglycerin, sodium
hyaluronate, disodium EDTA, sodium hydroxide,
ceramide NP, ceramide AP, phytosphingosine,
ceramide EOP, polyglyceryl-10
stearate, phytosterols, stearic acid,
pentylene glycol, aspartic acid, sodium
stearoyl glutamate.

WARNINGS

Avoid direct contact with eyes. If contact occurs rinse
throughly with water.